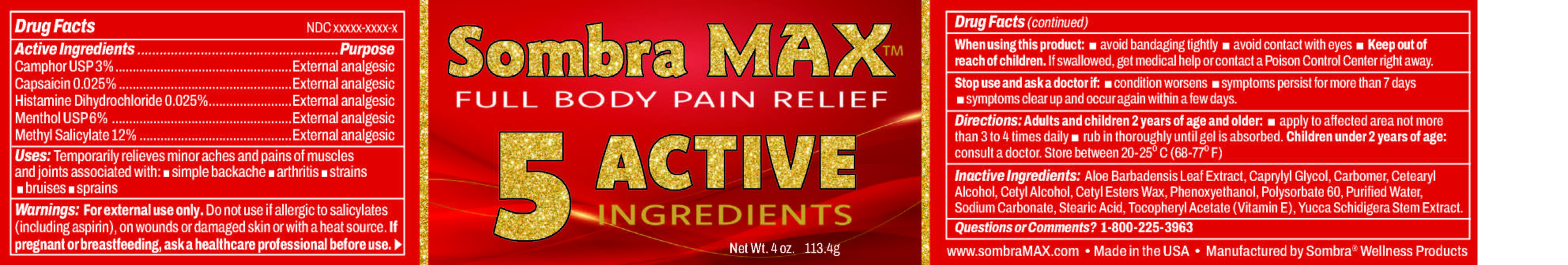 DRUG LABEL: Sombra Max
NDC: 61577-3440 | Form: CREAM
Manufacturer: Sombra Cosmetics Inc.
Category: otc | Type: HUMAN OTC DRUG LABEL
Date: 20251017

ACTIVE INGREDIENTS: MENTHOL GLUCURONIDE 6 g/100 g; HISTAMINE DIHYDROCHLORIDE 0.025 g/100 g; CAMPHOR (SYNTHETIC) 3 g/100 g; CAPSAICIN 0.025 g/100 g; METHYL SALICYLATE 12 g/100 g
INACTIVE INGREDIENTS: CETYL ESTERS

Active Ingredients Section OTC

Methyl Salicylate 12%

Menthol USP 6%

Camphor USP 3%

Capsaicin 0.025%

Histamine Dihydrochloride 0.025%

Purpose

External Analgesic

Uses

Temporarily relieves minor aches and pains of muscles and joints associated with simple backache, arthritis, strains, bruises, sprains

Warnings

For external use only. Do not use if allergic to salicylates (including aspirin), on wounds or damaged skin or with a heat source. When using this product: avoid bandaging tightly, avoid contact with eyes, keep out of reach of children. If swallowed, get medical help or contact a Posion Control Center right away.

Stop use and ask doctor if: condition worsens, symptoms persist for more than 7 days, clear up and occur again within a few days.

Keep out of reach of children, if swallowed get medical help or contact a Posion Control Center right away.

Directions

Directions: adults and children 2 years of age and older: apply to affected area not more than 3 to 4 times daily, rub in thoroughly until gel is absorbed, children under 2 years of age: consult a doctor.

Inactive Ingredients

Inactive Ingredients: Aloe Barbadensis Leaf Extract, Carbomer, Cetearyl Alcohol, Cetyl Esters, Caprylyl Glycol, Glycerin, Phenoxyethanol, Polysorbate 60, Purified Water, Sodium Carbonate, Stearic Acid, Tocopheryl Acetate (Vitamin E), Yucca Schidigera Stem Extract.

Questions

1-800-225-3963